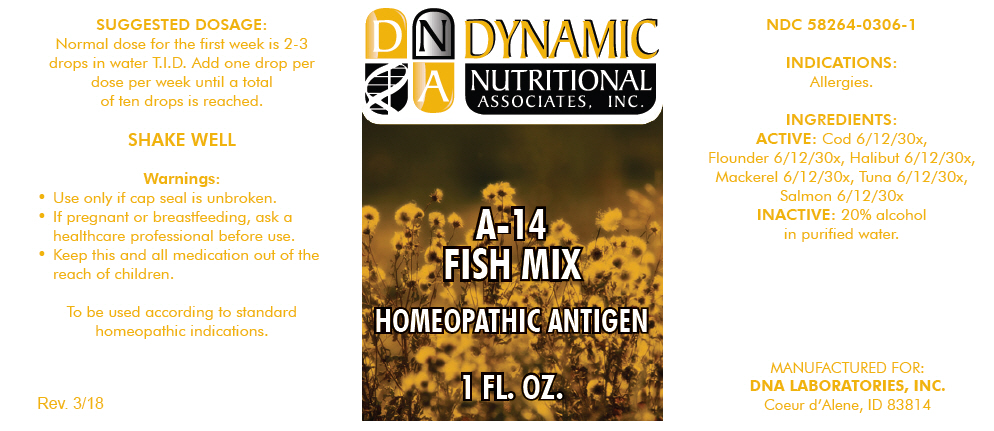 DRUG LABEL: A-14
NDC: 58264-0306 | Form: SOLUTION
Manufacturer: DNA Labs, Inc.
Category: homeopathic | Type: HUMAN OTC DRUG LABEL
Date: 20250109

ACTIVE INGREDIENTS: COD, UNSPECIFIED 30 [hp_X]/1 mL; FLOUNDER, UNSPECIFIED 30 [hp_X]/1 mL; HALIBUT, UNSPECIFIED 30 [hp_X]/1 mL; MACKEREL, UNSPECIFIED 30 [hp_X]/1 mL; TUNA, UNSPECIFIED 30 [hp_X]/1 mL; SALMON, UNSPECIFIED 30 [hp_X]/1 mL
INACTIVE INGREDIENTS: ALCOHOL; WATER

A-14

NDC 58264-0306-1

INDICATIONS

PURPOSE

Allergies.

INGREDIENTS

ACTIVE

Cod 6/12/30x, Flounder 6/12/30x, Halibut 6/12/30x, Mackerel 6/12/30x, Tuna 6/12/30x, Salmon 6/12/30x

INACTIVE

20% alcohol in purified water.

SUGGESTED DOSAGE

Normal dose for the first week is 2-3 drops in water T.I.D. Add one drop per dose per week until a total of ten drops is reached.

STORAGE AND HANDLING

SHAKE WELL

Warnings

- Use only if cap seal is unbroken.

PREGNANCY OR BREAST FEEDING

- If pregnant or breastfeeding, ask a healthcare professional before use.

KEEP OUT OF REACH OF CHILDREN

- Keep this and all medication out of the reach of children.

To be used according to standard homeopathic indications.

PRINCIPAL DISPLAY PANEL - 1 FL. OZ. Bottle Label

DYNAMIC
NUTRITIONAL
ASSOCIATES, INC.

A-14
FISH MIX

HOMEOPATHIC ANTIGEN

1 FL. OZ.